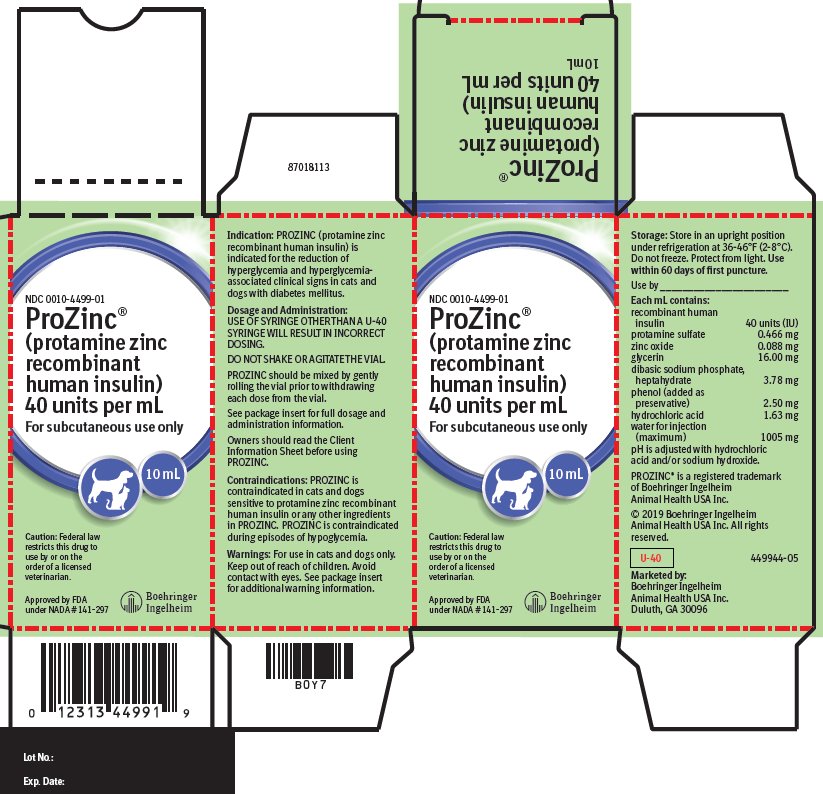 DRUG LABEL: ProZinc
NDC: 0010-4499 | Form: INJECTION
Manufacturer: Boehringer Ingelheim Animal Health USA Inc.
Category: animal | Type: PRESCRIPTION ANIMAL DRUG LABEL
Date: 20250122

ACTIVE INGREDIENTS: INSULIN HUMAN 40 [iU]/1 mL
INACTIVE INGREDIENTS: PROTAMINE SULFATE 0.466 mg/1 mL; ZINC OXIDE 0.088 mg/1 mL; GLYCERIN 16 mg/1 mL; SODIUM PHOSPHATE, DIBASIC, HEPTAHYDRATE 3.78 mg/1 mL; PHENOL 2.5 mg/1 mL; HYDROCHLORIC ACID 1.63 mg/1 mL; WATER 1005 mg/1 mL

ProZinc®
(protamine zinc recombinant human insulin) 40 IU/mL

Package Insert for Cats

ProZinc®

(protamine zinc recombinant human insulin)

40 IU/mL

Caution:

Federal law restricts this drug to use by or on the order of a licensed veterinarian.

Description:

PROZINC is a sterile aqueous protamine zinc suspension of recombinant human insulin.

Each mL contains:
recombinant human insulin............................40 International Units (IU)
protamine sulfate............................................0.466 mg
zinc oxide........................................................0.088 mg
glycerin...........................................................16.00 mg
dibasic sodium phosphate, heptahydrate........ 3.78 mg
phenol (added as preservative)....................... 2.50 mg
hydrochloric acid............................................ 1.63 mg
water for injection (maximum)....................... 1005 mg
pH is adjusted with hydrochloric acid and/or sodium hydroxide.

Indication:

PROZINC (protamine zinc recombinant human insulin) is indicated for the reduction of hyperglycemia and hyperglycemia-associated clinical signs in cats with diabetes mellitus.

Dosage and Administration:

USE OF A SYRINGE OTHER THAN A U-40 SYRINGE WILL RESULT IN INCORRECT DOSING.

FOR SUBCUTANEOUS INJECTION ONLY.

DO NOT SHAKE OR AGITATE THE VIAL.

PROZINC should be mixed by gently rolling the vial prior to withdrawing each dose from the vial. Once mixed, PROZINC suspension has a white, cloudy appearance. Clumps or visible white particles can form in insulin suspensions: do not use the product if clumps or visible white particles persist after gently rolling the vial.

Using a U-40 insulin syringe, the injection should be administered subcutaneously on the back of the neck or on the side of the cat.

Always provide the Client Information Sheet with each prescription.

The initial recommended PROZINC dose is 0.1 - 0.3 IU insulin/pound of body weight (0.2 - 0.7 IU/kg) every 12 hours. The dose should be given concurrently with or right after a meal. The veterinarian should re-evaluate the cat at appropriate intervals and adjust the dose based on both clinical signs and glucose nadirs until adequate glycemic control has been attained. In the effectiveness field study, glycemic control was considered adequate if the glucose nadir from a 9-hour blood glucose curve was between 80 and 150 mg/dL and clinical signs of hyperglycemia such as polyuria, polydipsia, and weight loss were improved.

Further adjustments in the dosage may be necessary with changes in the cat’s diet, body weight, or concomitant medication, or if the cat develops concurrent infection, inflammation, neoplasia, or an additional endocrine or other medical disorder.

Contraindications:

PROZINC is contraindicated in cats sensitive to protamine zinc recombinant human insulin or any other ingredients in PROZINC. PROZINC is contraindicated during episodes of hypoglycemia.

Warnings:

User Safety: For use in cats and dogs only. Keep out of the reach of children. Avoid contact with eyes. In case of contact, immediately flush eyes with running water for at least 15 minutes. Accidental injection may cause hypoglycemia. In case of accidental injection, seek medical attention immediately. Exposure to product may induce a local or systemic allergic reaction in sensitized individuals.

Animal Safety: Owners should be advised to observe for signs of hypoglycemia (see Client Information Sheet). Use of this product, even at established doses, has been associated with hypoglycemia. A cat with signs of hypoglycemia should be treated immediately. Glucose should be given orally or intravenously as dictated by clinical signs. Insulin should be temporarily withheld and, if indicated, the dosage adjusted.

Any change in insulin should be made cautiously and only under a veterinarian’s supervision. Changes in insulin strength, manufacturer, type, species (human, animal) or method of manufacture (rDNA versus animal-source insulin) may result in the need for a change in dosage.

Appropriate diagnostic tests should be performed to rule out other endocrinopathies in diabetic cats that are difficult to regulate.

Precautions:

Cats presenting with severe ketoacidosis, anorexia, lethargy, and/or vomiting should be stabilized with short-acting insulin and appropriate supportive therapy until their condition is stabilized. As with all insulin products, careful patient monitoring for hypoglycemia and hyperglycemia is essential to attain and maintain adequate glycemic control and to prevent associated complications. Overdose can result in profound hypoglycemia and death.

Glucocorticoids, progestogens, and certain endocrinopathies can have an antagonistic effect on insulin activity. Glucocorticoid and progestogen use should be avoided.

The safety and effectiveness of PROZINC in breeding, pregnant, and lactating cats has not been evaluated.

The safety and effectiveness of PROZINC in kittens has not been evaluated.

Adverse Reactions:

Effectiveness Field Study

In a 45-day effectiveness field study, 176 cats received PROZINC. Hypoglycemia (defined as a blood glucose value of < 50 mg/dL) occurred in 71 of the cats at various times throughout the study. Clinical signs of hypoglycemia were generally mild in nature (described as lethargic, sluggish, weak, trembling, uncoordinated, groggy, glassy-eyed or dazed). In 17 cases, the veterinarian provided oral glucose supplementation or food as treatment. Most cases were not associated with clinical signs and received no treatment. One cat had a serious hypoglycemic event associated with stupor, lateral recumbency, hypothermia and seizures.

All cases of hypoglycemia resolved with appropriate therapy and if needed, a dose reduction.

Three cats had injection site reactions which were described as either small, punctate, red lesions; lesions on neck; or palpable subcutaneous thickening. All injection site reactions resolved without cessation of therapy.

Four cats developed diabetic neuropathy during the study as evidenced by plantigrade stance. Three cats entered the study with plantigrade stance, one of which resolved by Day 45. Four cats were diagnosed with diabetic ketoacidosis during the study. Two were euthanized due to poor response to treatment. Five other cats were euthanized during the study, one of which had hypoglycemia. Four cats had received PROZINC for less than a week and were euthanized due to worsening concurrent medical conditions.

The following additional clinical observations or diagnoses were reported in cats during the effectiveness field study: vomiting, lethargy, diarrhea, cystitis/hematuria, upper respiratory infection, dry coat, hair loss, ocular discharge, abnormal vocalization, black stool, and rapid breathing.

Extended Use Field Study

Cats that completed the effectiveness study were enrolled into an extended use field study. In this study, 145 cats received PROZINC for up to an additional 136 days. Adverse reactions were similar to those reported during the 45-day effectiveness study and are listed in order of decreasing frequency: vomiting, hypoglycemia, anorexia/poor appetite, diarrhea, lethargy, cystitis/hematuria, and weakness. Twenty cats had signs consistent with hypoglycemia described as: sluggish, lethargic, unsteady, wobbly, seizures, trembling, or dazed. Most of these were treated by the owner or veterinarian with oral glucose supplementation or food; others received intravenous glucose. One cat had a serious hypoglycemic event associated with seizures and blindness. The cat fully recovered after supportive therapy and finished the study. All cases of hypoglycemia resolved with appropriate therapy and if needed, a dose reduction.

Fourteen cats died or were euthanized during the extended use study. In two cases, continued use of insulin despite anorexia and signs of hypoglycemia contributed to the deaths. In one case, the owner decided not to continue therapy after a presumed episode of hypoglycemia. The rest were due to concurrent medical conditions or worsening of the diabetes mellitus.

To report suspected adverse drug events, for technical assistance or to obtain a copy of the Safety Data Sheet (SDS), contact Boehringer Ingelheim at 1-888-637-4251.

For additional information about adverse drug experience reporting for animal drugs, contact FDA at 1-888-FDA-VETS or online at www.fda.gov/reportanimalae.

Information for Cat Owners:

Please refer to the Client Information Sheet for Cats for more information about PROZINC. PROZINC, like other insulin products, is not free from adverse reactions. Owners should be advised of the potential for adverse reactions and be informed of the associated clinical signs. Potential adverse reactions include: hypoglycemia, insulin antagonism/resistance, rapid insulin metabolism, insulin-induced hyperglycemia (Somogyi Effect), and local or systemic reactions. The most common adverse reaction observed is hypoglycemia. Signs may include: weakness, depression, behavioral changes, muscle twitching, and anxiety. In severe cases of hypoglycemia, seizures and coma can occur. Hypoglycemia can be fatal if an affected cat does not receive prompt treatment. Appropriate veterinary monitoring of blood glucose, adjustment of insulin dose and regimen as needed, and stabilization of diet and activity help minimize the risk of hypoglycemic episodes. The attending veterinarian should evaluate other adverse reactions on a case-by-case basis to determine if an adjustment in therapy is appropriate, or if alternative therapy should be considered.

Effectiveness:

A total of 187 client-owned cats were enrolled in a 45-day field study, with 176 receiving PROZINC. One hundred and fifty-one cats were included in the effectiveness analysis. The patients included various purebred and mixed breed cats ranging in age from 3 to 19 years and in weight from 4.6 to 20.8 pounds. Of the cats included in the effectiveness analysis, 101 were castrated males, 49 were spayed females, and 1 was an intact female.

Cats were started on PROZINC at a dose of 0.1-0.3 IU/lb (0.2-0.7 IU/kg) twice daily. Cats were evaluated at 7, 14, 30, and 45 days after initiation of therapy and the dose was adjusted based on clinical signs and results of 9-hour blood glucose curves on Days 7, 14, and 30.

Effectiveness was based on successful control of diabetes which was defined as improvement in at least one blood glucose variable (glucose curve mean, nadir, or fructosamine) and at least one clinical sign (polyuria, polydipsia, or body weight). Based on this definition, 115 of 151 cases (76.2%) were considered successful. Blood glucose curve means decreased from 415.3 mg/dL on Day 0 to 203.2 mg/dL by Day 45 and the mean blood glucose nadir decreased from 407.9 mg/dL on Day 0 to 142.4 mg/dL on Day 45. Mean fructosamine values decreased from 505.9 µmol/L on Day 0 to 380.7 µmol/L on Day 45.

Cats that completed the effectiveness study were enrolled in an extended use field study. The mean fructosamine value was 342.0 µmol/L after a total of 181 days of PROZINC therapy.

How Supplied:

PROZINC is supplied as a sterile injectable suspension in 10 mL and 20 mL multi-dose vials. Each mL of PROZINC contains 40 IU recombinant human insulin.

Storage Conditions:

Store in an upright position under refrigeration at 36-46°F (2-8°C). Do not freeze. Protect from light. Use the 10 mL vial within 60 days of first puncture. Use the 20 mL vial within 80 days of first puncture.

Approved by FDA under NADA #141-297

Marketed by:
Boehringer Ingelheim Animal Health USA Inc.
Duluth, GA 30096

PROZINC® is a registered trademark of Boehringer Ingelheim Animal Health USA Inc.

© 2019 Boehringer Ingelheim Animal Health USA Inc. All rights reserved.

Revised 08/2019
449986-01

Package Insert for Dogs

ProZinc®

(protamine zinc recombinant human insulin)

40 IU/mL

Caution:

Federal law restricts this drug to use by or on the order of a licensed veterinarian.

Description:

PROZINC is a sterile aqueous protamine zinc suspension of recombinant human insulin.

Each mL contains:
recombinant human insulin............................40 International Units (IU)
protamine sulfate............................................0.466 mg
zinc oxide........................................................0.088 mg
glycerin...........................................................16.00 mg
dibasic sodium phosphate, heptahydrate........ 3.78 mg
phenol (added as preservative)....................... 2.50 mg
hydrochloric acid............................................ 1.63 mg
water for injection (maximum)....................... 1005 mg
pH is adjusted with hydrochloric acid and/or sodium hydroxide.

Indication:

PROZINC (protamine zinc recombinant human insulin) is indicated for the reduction of hyperglycemia and hyperglycemia-associated clinical signs in dogs with diabetes mellitus.

Dosage and Administration:

USE OF A SYRINGE OTHER THAN A U-40 SYRINGE WILL RESULT IN INCORRECT DOSING.

FOR SUBCUTANEOUS INJECTION ONLY.

DO NOT SHAKE OR AGITATE THE VIAL.

PROZINC should be mixed by gently rolling the vial prior to withdrawing each dose from the vial. Once mixed, PROZINC suspension has a white, cloudy appearance. Clumps or visible white particles can form in insulin suspensions: do not use the product if clumps or visible white particles persist after gently rolling the vial.

Using a U-40 insulin syringe, the injection should be administered subcutaneously on the back of the neck or on the side of the dog.

Always provide the Client Information Sheet with each prescription.

Starting dose: The recommended starting dose for PROZINC is 0.2-0.5 IU insulin/pound of body weight (0.5-1.0 IU/kg) once daily. The recommended starting dose for naïve dogs is the lower end of the dose range. The recommended starting dose for dogs with poorly controlled diabetes mellitus and transitioning from another insulin product is the mid to higher end of the dose range based on the veterinarian’s experience with the dog’s medical history and previous insulin dose. When transitioning from another insulin, the dog’s blood glucose and general condition should be closely monitored. When transitioning from another insulin, PROZINC should be started once daily, regardless of the frequency of prior insulin use.

The dose should be given concurrently with or right after a meal. The veterinarian should re-evaluate the dog at appropriate intervals and adjust the dose and frequency based on both clinical signs and laboratory test results (the blood glucose curve values and shape, nadir, and fructosamine) until adequate glycemic control has been attained. In the effectiveness field study, glycemic control was considered adequate if the glucose nadir from a 9-hour blood glucose curve was between 80 and 125 mg/dL, the maximum blood glucose was ≤ 300 mg/dL, and clinical signs of hyperglycemia such as polyuria, polydipsia, or weight loss were improved.

Changing to twice daily dosing: Twice daily dosing should be considered if the duration of insulin action is determined to be inadequate with once daily dosing. Use caution when adjusting from once daily to twice daily dosing because PROZINC may have prolonged duration of action in some dogs (see Clinical Pharmacology). The veterinarian should closely monitor the duration of action using blood glucose curves to avoid the increased risk of hypoglycemia. If twice daily dosing is initiated, the two doses should each be approximately 25% less than the once daily dose required to attain an acceptable glucose nadir. For example, if a dog receiving 10 units of PROZINC once daily has an acceptable nadir but inadequate duration of activity, the dose should be changed to 7 units twice daily (round down to the nearest whole unit).

Further adjustments in the dosage may be necessary with changes in the dog’s diet, body weight, or concomitant medication, or if the dog develops concurrent infection, inflammation, neoplasia, or an additional endocrine or other medical disorder.

Contraindications:

PROZINC is contraindicated in dogs sensitive to protamine zinc recombinant human insulin or any other ingredients in PROZINC. PROZINC is contraindicated during episodes of hypoglycemia.

Warnings:

User Safety: For use in dogs and cats only. Keep out of the reach of children. Avoid contact with eyes. In case of contact, immediately flush eyes with running water for at least 15 minutes. Accidental injection may cause hypoglycemia. In case of accidental injection, seek medical attention immediately. Exposure to product may induce a local or systemic allergic reaction in sensitized individuals.

Animal Safety: Owners should be advised to observe for signs of hypoglycemia (see Client Information Sheet). Use of this product, even at established doses, has been associated with hypoglycemia. A dog with signs of hypoglycemia should be treated immediately. Glucose should be given orally or intravenously as dictated by clinical signs. Insulin should be temporarily withheld and, if indicated, the dosage adjusted.

Any change in insulin should be made cautiously and only under a veterinarian’s supervision. Changes in insulin strength, manufacturer, type, species (human, animal) or method of manufacture (rDNA versus animal-source insulin) may result in the need for a change in dosage.

Appropriate diagnostic tests should be performed to rule out other endocrinopathies in diabetic dogs that are difficult to regulate.

Precautions:

Dogs presenting with severe ketoacidosis, anorexia, lethargy, and/or vomiting should be stabilized with short-acting insulin and appropriate supportive therapy until their condition is stabilized. As with all insulin products, careful patient monitoring for hypoglycemia and hyperglycemia is essential to attain and maintain adequate glycemic control and to prevent associated complications. Overdose can result in profound hypoglycemia and death.

Glucocorticoids, progestogens, and certain endocrinopathies can have an antagonistic effect on insulin activity. Glucocorticoid and progestogen use should be avoided.

The safety and effectiveness of PROZINC in breeding, pregnant, and lactating dogs has not been evaluated.

The safety and effectiveness of PROZINC in puppies has not been evaluated.

Adverse Reactions:

In a 182-day field study, 276 dogs received PROZINC. The most common adverse reactions were lethargy, anorexia, hypoglycemia, vomiting, seizures, shaking, diarrhea, and ataxia.

Table 1 summarizes the adverse reactions reported in the study. Clinical signs of hypoglycemia varied and included seizure, collapse, ataxia, staggering, trembling, twitching, shaking, disorientation, lethargy, weakness, and vocalization. In Table 1, the individual clinical signs that were observed during the episodes of hypoglycemia are captured as separate adverse reactions and a single dog may have experienced more than one clinical sign of hypoglycemia.

Table 1. Adverse reactions seen in the safety population (276 dogs)

Adverse Reaction | Number and Percentage
Lethargy (lethargy, depression, listless, and tiredness) | 45 (16.3%)
Anorexia (anorexia, decreased appetite, inappetence, and not eating) | 28 (10.1%)
Hypoglycemia with clinical signs | 24 (8.9%)
Vomiting | 21 (7.6%)
Seizures | 16 (5.8%)
Shaking/trembling/twitching | 13 (4.7%)
Ataxia (ataxia, balance problem, stumbling gait) | 11 (4.0%)
Diarrhea (includes bloody diarrhea) | 9 (3.3%)
Disorientation/confusion | 9 (3.3%)
Weakness | 8 (2.9%)
Restlessness/anxiety/agitation | 6 (2.2%)
Cataract | 6 (2.2%)
Panting (panting and tachypnea) | 6 (2.2%)
Hematuria | 4 (1.5%)

Clinical pathology: The only change seen in complete blood count, serum chemistry, and urinalysis results was an elevation in mean cholesterol at Day 182 (432.6 mg/dL, normal range 131-345 mg/dL) compared to Day -1 (333.7 mg/dL).)

Injection site reactions: Seven dogs had injection site reactions, including observations of thickened skin, swelling, bumps at the injection site, and redness. All injection site reactions resolved without cessation of PROZINC therapy. Reaction to the injection, including vocalization, was observed in four dogs.

Hypoglycemia: There were 80 hypoglycemic episodes recorded during the study with some dogs experiencing more than one episode; 37 episodes were associated with clinical signs in 24 dogs, 40 episodes were without clinical signs in 27 dogs, and 3 were with unknown signs in 2 dogs. Clinical signs of hypoglycemia varied and included seizure, collapse, ataxia, staggering, trembling, twitching, shaking, disorientation, lethargy, weakness, and vocalization. Some dogs required hospitalization and intravenous dextrose while most recovered after receiving oral supplementation with a meal and/or oral glucose such as syrup. Two dogs were euthanized when the hypoglycemia did not resolve with supportive care. Hypoglycemia without clinical signs was defined as two consecutive blood glucose curve values < 60 mg/dL unaccompanied by clinical signs.

Diabetic ketoacidosis and pancreatitis: Eleven dogs were diagnosed with diabetic ketoacidosis. Four of these 11 dogs died or were euthanized, one after one dose of PROZINC. Twenty-one dogs were diagnosed with pancreatitis. Seven of these 21 dogs died or were euthanized due to

complications of pancreatitis. Four dogs had concurrent diabetic ketoacidosis and pancreatitis, three of which died or were euthanized. Not all the deaths were considered related to PROZINC.

Deaths: Thirty-six (36) dogs died or were euthanized, six of which were possibly related to PROZINC. One dog died from recurrent episodes of pancreatitis, and one died after developing severe vomiting and diarrhea followed by a seizure. Four dogs were euthanized: one developed severe pancreatitis and azotemia, one had recurrent episodes of pancreatitis and diabetic ketoacidosis, and two for lack of effectiveness.

To report suspected adverse drug events, for technical assistance or to obtain a copy of the Safety Data Sheet (SDS), contact Boehringer Ingelheim at 1-888-637-4251.

For additional information about adverse drug experience reporting for animal drugs, contact FDA at 1-888-FDA-VETS or online at www.fda.gov/reportanimalae.

Clinical Pharmacology:

PROZINC was administered subcutaneously to 10 healthy Beagles using an incomplete crossover design at doses of 0.5 IU/kg (5 dogs), 0.8 IU/kg at a single site (10 dogs), or 0.8 IU/kg at three separate sites (6 dogs). Insulin and glucose concentrations were measured over 24 hours. The shapes of insulin and glucose curves were variable among dogs; and the relationship between insulin dose, concentration, and glucose-lowering effect was nonlinear (Table 2).

Table 2. Pharmacodynamics of three dosing groups

Dose group | Onset of Action | Time to nadir | Duration of Action
0.5 IU/kg at a single site | 1 to 14 hours | 6 to 16 hours | 16 to >24 hours
0.8 IU/kg at a single site | 0.5 to 10 hours | 5 to >24 hours | 16 to >24 hours
0.8 IU/kg divided at three sites | 1 to 10 hours | 8 to 20 hours | 18 to >24 hours

Information for Dog Owners:

Please refer to the Client Information Sheet for Dogs for more information about PROZINC. PROZINC, like other insulin products, is not free from adverse reactions. Owners should be advised of the potential for adverse reactions and be informed of the associated clinical signs. Potential adverse reactions include hypoglycemia, insulin antagonism/resistance, rapid insulin metabolism, insulin-induced hyperglycemia (Somogyi Effect), and local or systemic reactions. The most common adverse reaction observed is hypoglycemia. Signs may include weakness, depression, behavioral changes, muscle twitching, and anxiety. In severe cases of hypoglycemia, seizures and coma can occur. Hypoglycemia can be fatal if an affected dog does not receive prompt treatment. Appropriate veterinary monitoring of blood glucose, adjustment of insulin dose and regimen as needed, and stabilization of diet and activity help minimize the risk of hypoglycemic episodes. The attending veterinarian should evaluate other adverse reactions on a case-by-case basis to determine if an adjustment in therapy is appropriate, or if alternative therapy should be considered.

Effectiveness:

A total of 276 client-owned dogs were enrolled in an 84-day field study followed by a 98-day extended-use phase with 276 dogs receiving PROZINC. The dogs included various purebred and mixed breed dogs ranging in age from 2 to 16 years and in weight from 3.3 to 123 pounds. There were 128 neutered males, 8 intact males, 134 spayed females and 6 intact females. Two hundred twenty-four dogs (224) were included in the effectiveness analysis. Dogs were started on PROZINC at a dose of 0.2-0.5 IU/lb (0.5-1.0 IU/kg) once daily. Dogs were evaluated at 7, 14, 21, 28, 42, 63 and 84 days after initiation of therapy. The dose was adjusted based on clinical signs and results of 9-hour blood glucose curves on Days 7, 14, 21, 28, 42, 63 and 84.

Effectiveness was based on successful control of diabetes which was defined as improvement in at least one laboratory variable (blood glucose curve mean, blood glucose curve nadir, or fructosamine) and at least one clinical sign (polyuria, polydipsia, or weight loss). Based on this definition, 162 of 224 cases (72%) were considered successful.

How Supplied:

PROZINC is supplied as a sterile injectable suspension in 10 mL and 20 mL multi-dose vials. Each mL of PROZINC contains 40 IU recombinant human insulin.

Storage Conditions:

Store in an upright position under refrigeration at 36-46°F (2-8°C). Do not freeze. Protect from light. Use the 10 mL vial within 60 days of first puncture. Use the 20 mL within 80 days of first puncture.

Approved by FDA under NADA #141-297

Marketed by:
Boehringer Ingelheim Animal Health USA Inc.
Duluth, GA 30096

PROZINC® is a registered trademark of Boehringer Ingelheim Animal Health USA Inc.

© 2019 Boehringer Ingelheim Animal Health USA Inc. All rights reserved.

Revised 08/2019
449986-01

Client Information Sheet for Cats

ProZinc®

(protamine zinc recombinant human insulin) 40 IU/mL

This summary contains important information about PROZINC. You should read this information before you start giving your cat PROZINC and review it each time the prescription is refilled. This sheet is provided only as a summary and does not take the place of instructions from your veterinarian. Talk to your veterinarian if you do not understand any of this information or if you want to know more about PROZINC.

What is PROZINC?

PROZINC is an aqueous protamine zinc suspension of recombinant human insulin that is used to reduce high blood sugar (hyperglycemia) in cats with diabetes mellitus. A veterinarian must prescribe PROZINC for your cat. PROZINC should be given only to the cat for which it is prescribed. Keep out of reach of children. Seek medical attention immediately if you accidentally inject yourself with PROZINC.

What is diabetes mellitus?

Diabetes mellitus occurs when a cat has insufficient levels of, or an abnormal response to, insulin. The low insulin levels may result in high blood sugar (hyperglycemia) that could produce the following changes in your cat:
• Increased thirst
• Increased urination
• Increased appetite
• Weight loss
• High levels of sugar (glucose) in the urine (glucosuria)
• Weakness in the back legs

What kind of results can I expect when my cat is on PROZINC for diabetes mellitus?

Although PROZINC is not a cure for diabetes mellitus, it can help reduce the levels of sugar (glucose) in the blood, which can help alleviate the clinical signs.

What should I discuss with my veterinarian before giving PROZINC?

Talk to your veterinarian about:
• The signs of diabetes mellitus you have observed in your cat (for example, increased thirst and urination).
• The importance of proper PROZINC storage, handling, and administration techniques (for example, how to gently roll the vial prior to each use, the proper appearance of product after gently rolling, how to fill the U-40 syringe with the proper amount of insulin, and where and how to inject the insulin).
• The importance of maintaining your cat under the same conditions for diet, exercise, environment, etc.
• The importance of follow-up visits for testing to determine if dose adjustments of PROZINC are necessary.
Tell your veterinarian about:
• Any side effects your cat has had when receiving other insulin products.
• Any medical problems or allergies that your cat has now or has had in the past.
• All medications that you are giving your cat or plan to give your cat, including those you can get without a prescription.
• If your cat is pregnant, nursing, or if you plan to breed your cat.

What are the possible side effects that may occur in my cat during PROZINC therapy?

PROZINC, like other drugs, may cause side effects. Serious side effects can occur with or without warning. Please contact your veterinarian immediately if you think your cat has a medical problem or side effect from PROZINC therapy. The most common insulin-related side effect is low blood sugar (hypoglycemia). Signs of low blood sugar (hypoglycemia) can occur suddenly and may include:
• Weakness
• Depression, lethargy, sluggishness
• Staggering gait
• Behavioral changes
• Muscle twitching
• Seizures, convulsions
• Coma
• Death

What actions do I take if my cat shows signs of low blood sugar (hypoglycemia)?

• If your cat is unconscious or having a seizure, this is a medical emergency. Take your cat to the veterinarian immediately.
• If your cat is conscious, rub approximately 1 tablespoon of corn syrup or honey on your cat’s gums. When it is able to swallow, give corn syrup or honey by mouth until your cat is alert enough to eat. Feed the usual meal and contact your veterinarian.

When should my cat not be given PROZINC?

Do not give your cat its prescribed dose of PROZINC if it:
• Is experiencing an episode of low blood sugar (hypoglycemia). Common causes for low blood sugar include excessive doses of insulin, failure to eat, strenuous exercise, changes in the body’s need for insulin, diabetes-inducing disease or drug effects.
• Is not eating or is vomiting.
• Is sensitive to protamine zinc recombinant human insulin or any other ingredients in PROZINC.

• Do not give your cat its prescribed dose of PROZINC if you see clumps or visible white particles in the vial after gently rolling.

How should I give PROZINC to my cat?

PROZINC should be given with or right after a meal.

Give PROZINC with U-40 syringes only. Use of a syringe other than a U-40 syringe will result in incorrect dosing. Gently roll the vial until the PROZINC has a uniformly cloudy, white appearance. If there are clumps or visible white particles in the vial after gently rolling, do not use the PROZINC and call your veterinarian. PROZINC should be given according to your veterinarian’s instructions. Your veterinarian will tell you what amount of PROZINC is right for your cat and instruct you on techniques for administration.

Can PROZINC be given with other medications?

PROZINC can be given with other medications, but the dose may need to be adjusted due to the medication resulting in either increased or decreased insulin requirements. Tell your veterinarian about all medications you have given your cat in the past, and any medications that you are planning to give with PROZINC. This should include medications that you can get for your cat without a prescription. Your veterinarian may want to ensure that all of your cat’s medications can be given together.

What should I do if I inject more than the prescribed amount of PROZINC?

Contact your veterinarian immediately and, if your veterinarian is not available, seek other veterinary advice at once.

What should I do if my cat receives less than the prescribed dose, or I miss an injection?

• Contact your veterinarian as soon as possible for advice on your cat’s next dose.
• If you cannot reach your veterinarian and your cat is eating and acting normally, give your cat the usual dose at the next regularly scheduled injection time.

How should I store PROZINC?

PROZINC should be stored in an upright position under refrigeration at 36-46°F (2-8°C). Do not freeze. Protect from light. Use the 10 mL vial within 60 days of first puncture. Use the 20 mL vial within 80 days of first puncture.

What else should I know about PROZINC?

This sheet provides a summary of information about PROZINC. If you have any questions or concerns about the product or diabetes mellitus, talk to your veterinarian.
As with all prescribed medications, PROZINC should only be given to the cat for which it is prescribed and for the condition for which it was prescribed.
It is important to periodically discuss your cat’s response to PROZINC at regular checkups that may include blood glucose monitoring. Your veterinarian will best determine if your cat is responding as expected and should continue receiving PROZINC.

Approved by FDA under NADA # 141-297

PROZINC® is a registered trademark of Boehringer Ingelheim Animal Health USA Inc.

© 2019 Boehringer Ingelheim Animal Health USA Inc. All rights reserved.

Revised 08/2019

Client Information Sheet for Dogs

ProZinc®

(protamine zinc recombinant human insulin)

40 IU/mL

This summary contains important information about PROZINC. You should read this information before you start giving your dog PROZINC and review it each time the prescription is refilled. This sheet is provided only as a summary and does not take the place of instructions from your veterinarian. Talk to your veterinarian if you do not understand any of this information or if you want to know more about PROZINC.

What is PROZINC?

PROZINC is an aqueous protamine zinc suspension of recombinant human insulin that is used to reduce high blood sugar (hyperglycemia) in dogs with diabetes mellitus. A veterinarian must prescribe PROZINC for your dog. PROZINC should be given only to the dog for which it is prescribed. Keep out of reach of children. Seek medical attention immediately if you accidentally inject yourself with PROZINC.

What is diabetes mellitus?

Diabetes mellitus occurs when a dog has insufficient levels of, or an abnormal response to, insulin. The low insulin levels may result in high blood sugar (hyperglycemia) that could produce the following changes in your dog:
• Increased thirst
• Increased urination
• Increased appetite
• Weight loss
• High levels of sugar (glucose) in the urine (glucosuria)

What kind of results can I expect when my dog is on PROZINC for diabetes mellitus?

Although PROZINC is not a cure for diabetes mellitus, it can help reduce the levels of sugar (glucose) in the blood, which can help alleviate the clinical signs.

What should I discuss with my veterinarian before giving PROZINC?

Talk to your veterinarian about:
• The signs of diabetes mellitus you have observed in your dog (for example, increased thirst and urination).
• The importance of proper PROZINC storage, handling, and administration techniques (for example, how to gently roll the vial prior to each use, the proper appearance of product after gently rolling, how to fill the U-40 syringe with the proper amount of insulin, and where and how to inject the insulin).
• The importance of maintaining your dog under the same conditions for diet, exercise, environment, etc.
• The importance of follow-up visits for testing to determine if dose adjustments of PROZINC are necessary.

Tell your veterinarian about:
• Any side effects your dog has had when receiving other insulin products.
• Any medical problems or allergies that your dog has now or has had in the past.
• All medications that you are giving your dog or plan to give your dog, including those you can get without a prescription.
• If your dog is pregnant, nursing, or if you plan to breed your dog.

What are the possible side effects that may occur in my dog during PROZINC therapy?

PROZINC, like other drugs, may cause side effects. Serious side effects can occur with or without warning. Please contact your veterinarian immediately if you think your dog has a medical problem or side effect from PROZINC therapy. The most common insulin-related side effect is low blood sugar (hypoglycemia). Signs of low blood sugar (hypoglycemia) can occur suddenly and may include:
• Weakness
• Depression, lethargy, sluggishness
• Staggering gait
• Behavioral changes
• Muscle twitching
• Seizures, convulsions
• Coma
• Death

What actions do I take if my dog shows signs of low blood sugar (hypoglycemia)?

• If your dog is unconscious or having a seizure, this is a medical emergency. Take your dog to the veterinarian immediately.
• If your dog is conscious, rub approximately 1 tablespoon of corn syrup or honey on your dog’s gums. When it can swallow, give corn syrup or honey by mouth until your dog is alert enough to eat. Feed the usual meal and contact your veterinarian.

When should my dog not be given PROZINC?

Do not give your dog its prescribed dose of PROZINC if it:
• Is experiencing an episode of low blood sugar (hypoglycemia). Common causes for low blood sugar include excessive doses of insulin, failure to eat, strenuous exercise, changes in the body’s need for insulin, diabetes-inducing disease or drug effects.
• Is not eating or is vomiting.
• Is sensitive to protamine zinc recombinant human insulin or any other ingredients in PROZINC.

• Do not give your dog its prescribed dose of PROZINC if you see clumps or visible white particles in the vial after gently rolling.

How should I give PROZINC to my dog?

PROZINC should be given with or right after a meal.

Give PROZINC with U-40 syringes only. Use of a syringe other than a U-40 syringe will result in incorrect dosing. Gently roll the vial until the PROZINC has a uniformly cloudy, white appearance. If there are clumps or visible white particles in the vial after gently rolling, do not use the PROZINC and call your veterinarian. PROZINC should be given according to your veterinarian’s instructions. Your veterinarian will tell you what amount of PROZINC is right for your dog and instruct you on techniques for administration.

Can PROZINC be given with other medications?

PROZINC can be given with other medications, but the dose may need to be adjusted due to the medication resulting in either increased or decreased insulin requirements. Tell your veterinarian about all medications you have given your dog in the past, and any medications that you are planning to give with PROZINC. This should include medications that you can get for your dog without a prescription. Your veterinarian may want to ensure that all your dog’s medications can be given together.

What should I do if I inject more than the prescribed amount of PROZINC?

Contact your veterinarian immediately and, if your veterinarian is not available, seek other veterinary advice at once.

What should I do if my dog receives less than the prescribed dose, or I miss an injection?

• Contact your veterinarian as soon as possible for advice on your dog’s next dose.
• If you cannot reach your veterinarian and your dog is eating and acting normally, give your dog the usual dose at the next regularly scheduled injection time.

How should I store PROZINC?

PROZINC should be stored in an upright position under refrigeration at 36-46°F (2-8°C). Do not freeze. Protect from light. Use the 10 vial within 60 days of first puncture. Use the 20 mL vial within 80 days of first puncture.

What else should I know about PROZINC?

This sheet provides a summary of information about PROZINC. If you have any questions or concerns about the product or diabetes mellitus, talk to your veterinarian.
As with all prescribed medications, PROZINC should only be given to the dog for which it is prescribed and for the condition for which it was prescribed.
It is important to periodically discuss your dog’s response to PROZINC at regular checkups that may include blood glucose monitoring. Your veterinarian will best determine if your dog is responding as expected and should continue receiving PROZINC.

Approved by FDA under NADA # 141-297

PROZINC® is a registered trademark of Boehringer Ingelheim Animal Health USA Inc.

© 2019 Boehringer Ingelheim Animal Health USA Inc. All rights reserved.

Revised 08/2019